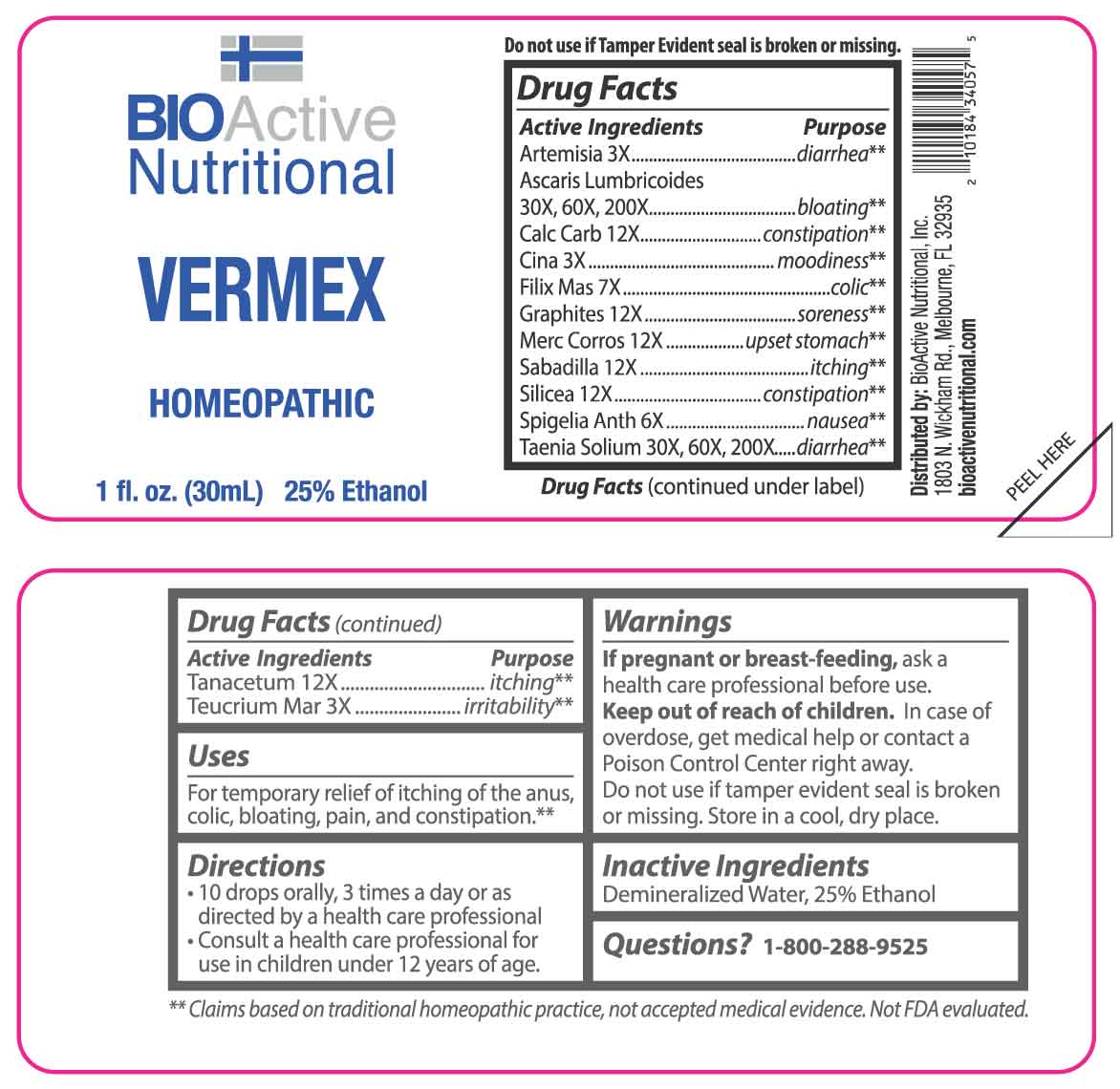 DRUG LABEL: Vermex
NDC: 43857-0660 | Form: LIQUID
Manufacturer: BioActive Nutritional, Inc.
Category: homeopathic | Type: HUMAN OTC DRUG LABEL
Date: 20251230

ACTIVE INGREDIENTS: ARTEMISIA VULGARIS ROOT 3 [hp_X]/1 mL; ARTEMISIA CINA PRE-FLOWERING TOP 3 [hp_X]/1 mL; TEUCRIUM MARUM WHOLE 3 [hp_X]/1 mL; SPIGELIA ANTHELMIA WHOLE 6 [hp_X]/1 mL; DRYOPTERIS FILIX-MAS ROOT 7 [hp_X]/1 mL; OYSTER SHELL CALCIUM CARBONATE, CRUDE 12 [hp_X]/1 mL; GRAPHITE 12 [hp_X]/1 mL; MERCURIC CHLORIDE 12 [hp_X]/1 mL; SCHOENOCAULON OFFICINALE SEED 12 [hp_X]/1 mL; SILICON DIOXIDE 12 [hp_X]/1 mL; TANACETUM VULGARE TOP 12 [hp_X]/1 mL; ASCARIS LUMBRICOIDES 30 [hp_X]/1 mL; TAENIA SOLIUM 30 [hp_X]/1 mL
INACTIVE INGREDIENTS: WATER; ALCOHOL

DRUG FACTS:

ACTIVE INGREDIENTS:

Artemisia Vulgaris 3X, Ascaris Lumbricoides 30X, 60X, 200X, Calcarea Carbonica 12X, Cina 3X, Filix Mas 7X, Graphites 12X, Mercurius Corrosivus 12X, Sabadilla 12X, Silicea 12X, Spigelia Anthelmia 6X, Taenia Solium 30X, 60X, 200X, Tanacetum Vulgare 12X, Teucrium Marum 3X.

PURPOSE:

Artemisia Vulgaris - diarrhea,** Ascaris Lumbricoides - bloating,** Calcarea Carbonica - constipation,** Cina - moodiness,** Filix Mas - colic,** Graphites - soreness,** Mercurius Corrosivus – upset stomach,** Sabadilla - itching,** Silicea - constipation,** Spigelia Anthelmia - nausea,** Taenia Solium - diarrhea,** Tanacetum Vulgare - itching,** Teucrium Marum – irritability**

**Claims based on traditional homeopathic practice, not accepted medical evidence. Not FDA evaluated.

USES:

For temporary relief of itching of the anus, colic, bloating, pain, and constipation.**

**Claims based on traditional homeopathic practice, not accepted medical evidence. Not FDA evaluated.

WARNINGS:

If pregnant or breast-feeding, ask a health care professional before use.

Keep out of reach of children. In case of overdose, get medical help or contact a Poison Control Center right away.

Do not use if tamper evident seal is broken or missing.

Store in a cool, dry place.

KEEP OUT OF REACH OF CHILDREN:

In case of overdose, get medical help or contact a Poison Control Center right away.

DIRECTIONS:

• 10 drops orally, 3 times a day or as directed by a health care professional.

• Consult a health care professional for use in children under 12 years of age.

INACTIVE INGREDIENTS:

Demineralized Water, 25% Ethanol

QUESTIONS:

Distributed by:
BioActive Nutritional, Inc.
1803 N. Wickham Rd.
Melbourne, FL 32935
bioactivenutritional.com

1-800-288-9525

PACKAGE LABEL DISPLAY:

BIOActive Nutritional

VERMEX

HOMEOPATHIC

1 fl. oz. (30 mL)